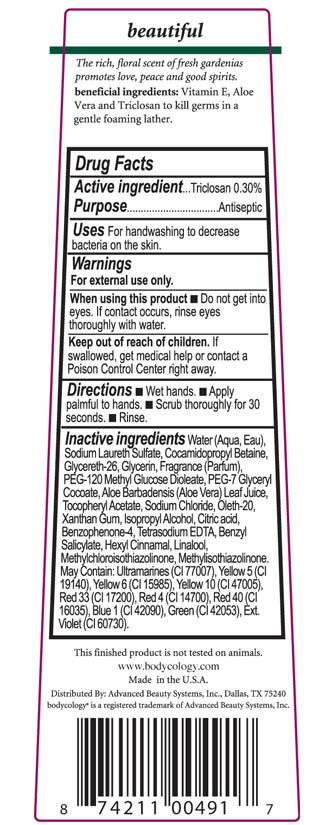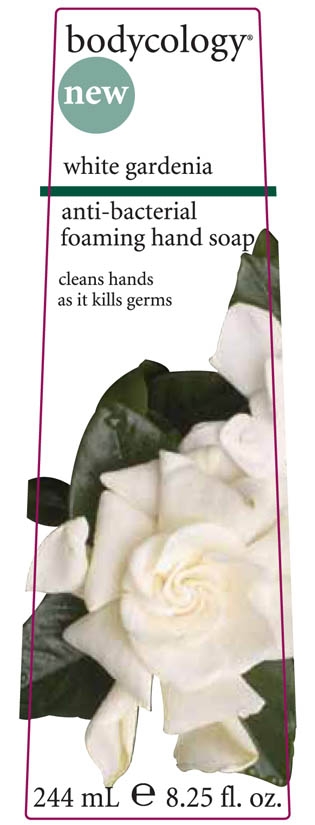 DRUG LABEL: Bodycology white gardenia anti-bacterial foaming hand soap
NDC: 65663-020 | Form: LIQUID
Manufacturer: American Blending and Filling
Category: otc | Type: HUMAN OTC DRUG LABEL
Date: 20100420

ACTIVE INGREDIENTS: Triclosan .30 mL/100 mL

Drug Facts

Active Ingredient

Triclosan

Purpose Antiseptic

Uses For handwashing to decrease bacteria on the skin.

Warnings For external use only

WHEN USING

Do not get into eyes. If contact occurs, rinse eyes throughly with water.

Keep out of reach of children. If swallowed, get medical help or contact a Poison Control Center right away.

Directions Wet hands. Apply palmful to hands. Scrub thoroughly for 30 seconds. Rinse.

INACTIVE INGREDIENT

Inactive Ingredients Water (Aqua, Eau), Sodium Laureth Sulfate, Cocamidopropyl Betaine, Glycereth-26, Glycerine, Fragrance (Parfum), PEG-120 Methyl Glucose Dioleate, PEG-7 Glyceryl Cocoate, Aloe Barbadensis (Aloe Vera) Leaf Juice, Tocopheryl Acetate, Sodium Chloride, Oleth-20, Xanthan Gum, Isopropyl Alcohol, Citric acid, Benzophenone-4, Tetrasodium EDTA, Benzyl Salicylate, Hexyl Cinnamal, Linalool, Methylchloroisothiazolinone, Methylisothaizolinone. May Contain: Ultramarines (Cl 77007), Yellow 5 (Cl 19140), Yellow 6 (CL 15985), Yellow 10 (Cl 47005), Red 33 (Cl 17200), Red 4 (Cl 14700), Red 40 (Cl 16035), Blue 1 (Cl 42090), Green (Cl 42053), Ext. Violet (Cl 60730).